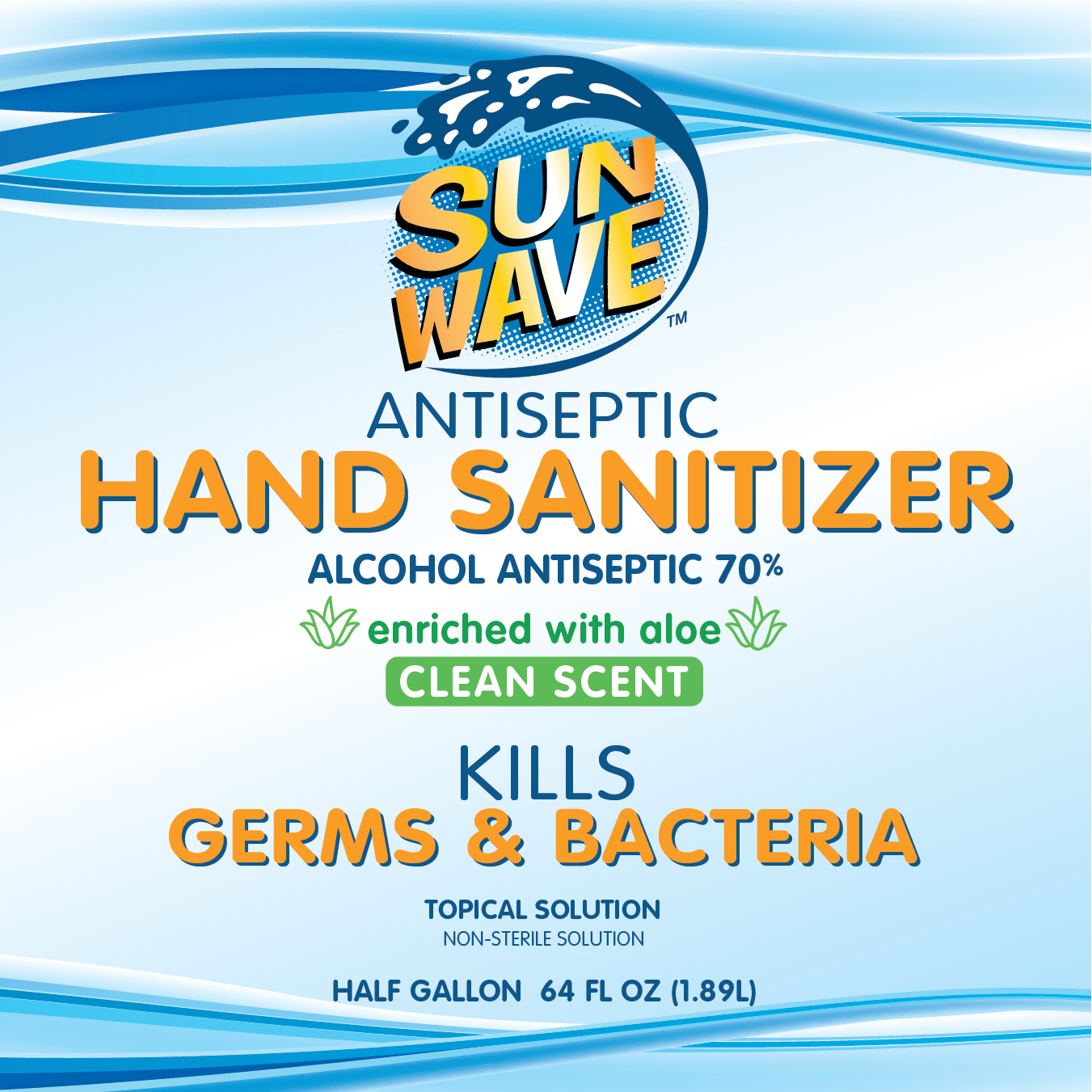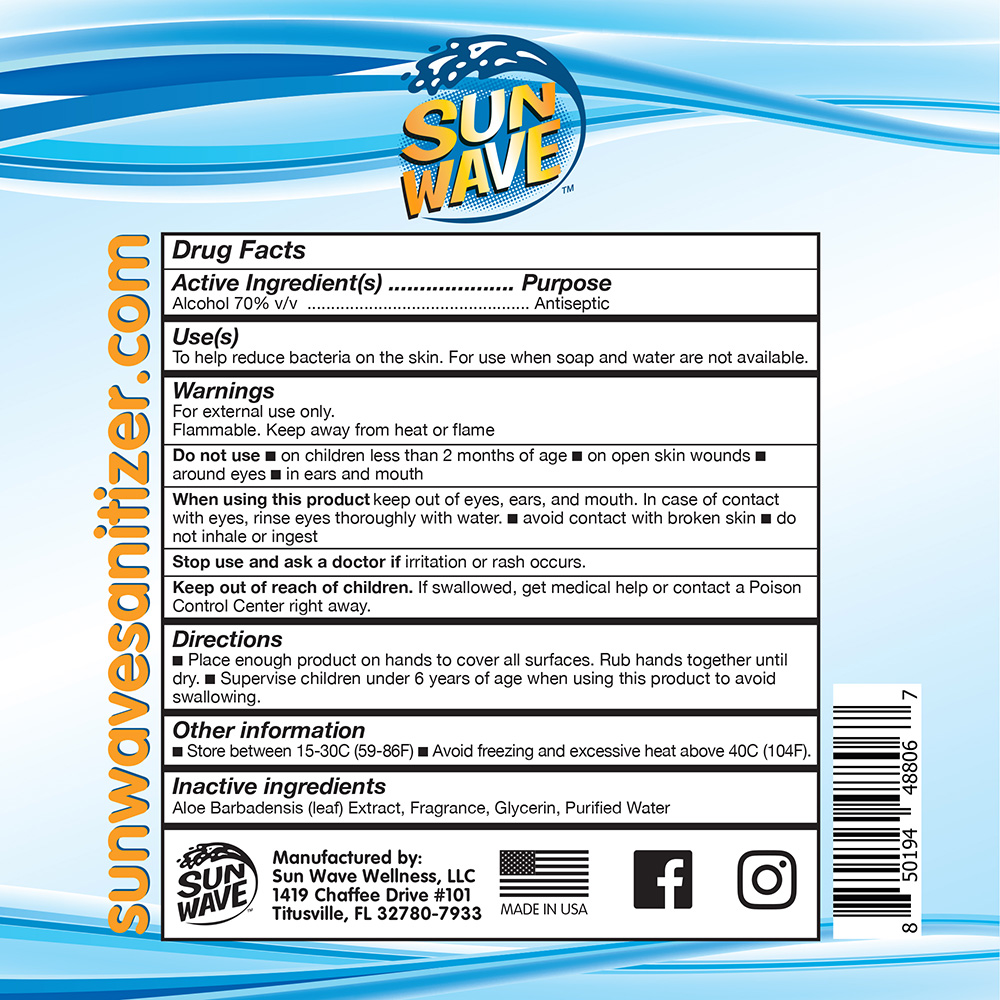 DRUG LABEL: HAND SANITIZER
NDC: 75023-003 | Form: LIQUID
Manufacturer: SUN WAVE WELLNESS, LLC
Category: otc | Type: HUMAN OTC DRUG LABEL
Date: 20200826

ACTIVE INGREDIENTS: ISOPROPYL ALCOHOL 1.325 L/1.893 L
INACTIVE INGREDIENTS: WATER 0.492 L/1.893 L; ALOE VERA LEAF 0.019 L/1.893 L; GLYCERIN 0.038 L/1.893 L; LIMONENE, (+)- 0.019 L/1.893 L

VERSION 2: CORRECTION INTENDED TO REPLACE SETID SUBMISSION ENDING "..AB88E"
CORRECTION: (1) BACK LABEL REPLACEMENT
CONSUMER HAND SANITIZER; NON-EMERGENCY; ISOPROPYL ALCOHOL = DEFERRED GRASE ACTIVE INGREDIENT DETERMINATION EFFECTIVE APRIL 13, 2020; PART333E FOR OTC HAND RUB SANITIZERS (CONSUMER)

Active Ingredient(s)

Alcohol 70% v/v

Purpose

Antiseptic

Use(s)

To help reduce bacteria on the skin. For use when soap and water are not available.

Warnings

For external use only.

Flammable. Keep away from heat or flame.

Do not use

- on children less than 2 months of age
- on open skin wounds
- around eyes
- in ears and mouth

When using this product

keep out of eyes, ears, and mouth. In case of contact with eyes, rinse eyes thoroughly with water.

- avoid contact with broken skin
- do not inhale or ingest

Stop use and ask a doctor if

irritation or rash occurs.

Keep out of reach of children.

If swallowed, get medical help or contact a Poison Control Center right away.

Directions

- Place enough product on hands to cover all surfaces. Rub hands together until dry.
- Supervise children under 6 years of age when using this product to avoid swallowing.

Other information

- Store between 15-30C (59-86F)
- Avoid freezing or excessive heat above 40C (104F).

Inactive ingredients

Aloe Barbadensis (leaf) Extract, Fragrance, Glycerin, Purified Water

Manufactured by:

Sun Wave Wellness, LLC

1419 Chaffee Drive #101

Titusville, FL 32780-7933